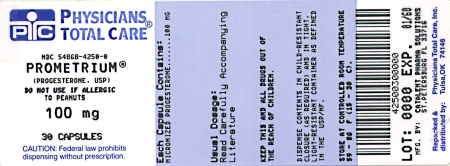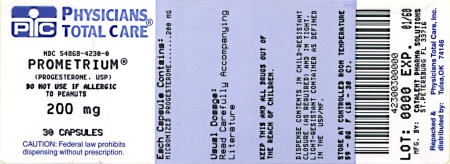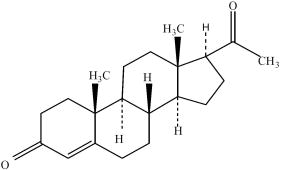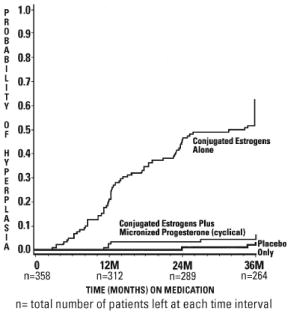 DRUG LABEL: Prometrium
NDC: 54868-4250 | Form: CAPSULE
Manufacturer: Physicians Total Care, Inc.
Category: prescription | Type: HUMAN PRESCRIPTION DRUG LABEL
Date: 20100824

ACTIVE INGREDIENTS: PROGESTERONE 100 mg/1 1
INACTIVE INGREDIENTS: PEANUT OIL; GELATIN; GLYCERIN; TITANIUM DIOXIDE; D&C YELLOW NO. 10; FD&C RED NO. 40

Rx Only

500032 Rev Jan 2008

WARNINGS

Progestins and estrogens should not be used for the prevention of cardiovascular disease. (See WARNINGS, Cardiovascular Disorders.)

The Women's Health Initiative (WHI) study reported increased risks of myocardial infarction, stroke, invasive breast cancer, pulmonary emboli, and deep vein thrombosis in postmenopausal women (50 to 79 years of age) during 5 years of treatment with oral conjugated estrogens (CE 0.625 mg) combined with medroxyprogesterone acetate (MPA 2.5 mg) relative to placebo. (See CLINICAL PHARMACOLOGY, Clinical Studies.)

The Women's Health Initiative Memory Study (WHIMS), a substudy of WHI, reported increased risk of developing probable dementia in postmenopausal women 65 years of age or older during 4 years of treatment with oral conjugated estrogens plus medroxyprogesterone acetate relative to placebo. It is unknown whether this finding applies to younger postmenopausal women. (See CLINICAL PHARMACOLOGY, Clinical Studies.)

Other doses of oral conjugated estrogens with medroxyprogesterone and other combinations and dosage forms of estrogens and progestins were not studied in the WHI clinical trials. In the absence of comparable data and product-specific studies, the relevance of the WHI findings to other products has not been established. Therefore, the risks should be assumed to be similar for all estrogen and progestin products. Because of these risks, estrogens with or without progestins should be prescribed at the lowest effective doses and for the shortest duration consistent with treatment goals and risks for the individual woman.

DESCRIPTION

PROMETRIUM® (progesterone, USP) Capsules contain micronized progesterone for oral administration. Progesterone has a molecular weight of 314.47 and a molecular formula of C21H30O2. Progesterone (pregn-4-ene-3, 20-dione) is a white or creamy white, odorless, crystalline powder practically insoluble in water, soluble in alcohol, acetone and dioxane and sparingly soluble in vegetable oils, stable in air, melting between 126° and 131°C. The structural formula is:

Progesterone is synthesized from a starting material from a plant source and is chemically identical to progesterone of human ovarian origin. PROMETRIUM Capsules are available in multiple strengths to afford dosage flexibility for optimum management. PROMETRIUM Capsules contain 100 mg or 200 mg micronized progesterone.

The inactive ingredients for PROMETRIUM Capsules 100 mg include: peanut oil NF, gelatin NF, glycerin USP, lecithin NF, titanium dioxide USP, D&C Yellow No. 10, and FD&C Red No. 40.

The inactive ingredients for PROMETRIUM Capsules 200 mg include: peanut oil NF, gelatin NF, glycerin USP, lecithin NF, titanium dioxide USP, D&C Yellow No. 10, and FD&C Yellow No. 6.

CLINICAL PHARMACOLOGY

PROMETRIUM Capsules are an oral dosage form of micronized progesterone which is chemically identical to progesterone of ovarian origin. The oral bioavailability of progesterone is increased through micronization.

Pharmacokinetics

Absorption: After oral administration of progesterone as a micronized soft-gelatin capsule formulation, maximum serum concentrations were attained within 3 hours. The absolute bioavailability of micronized progesterone is not known. Table 1 summarizes the mean pharmacokinetic parameters in postmenopausal women after five oral daily doses of PROMETRIUM Capsules 100 mg as a micronized soft-gelatin capsule formulation.

TABLE 1
Parameter | PROMETRIUM Capsules Daily Dose
100 mg | 200 mg | 300 mg
Cmax (ng/mL) | 17.3 ± 21.9a | 38.1 ± 37.8 | 60.6 ± 72.5
Tmax (hr) | 1.5 ± 0.8 | 2.3 ± 1.4 | 1.7 ± 0.6
AUC (0-10) (ng•hr/mL) | 43.3 ± 30.8 | 101.2 ± 66.0 | 175.7 ± 170.3

a Mean ± S.D.

Serum progesterone concentrations appeared linear and dose proportional following multiple dose administration of PROMETRIUM Capsules 100 mg over the dose range 100 mg/day to 300 mg/day in postmenopausal women. Although doses greater than 300 mg/day were not studied in females, serum concentrations from a study in male volunteers appeared linear and dose proportional between 100 mg/day and 400 mg/day. The pharmacokinetic parameters in male volunteers were generally consistent with those seen in postmenopausal women.

Distribution: Progesterone is approximately 96% to 99% bound to serum proteins, primarily to serum albumin (50% to 54%) and transcortin (43% to 48%).

Metabolism: Progesterone is metabolized primarily by the liver largely to pregnanediols and pregnanolones. Pregnanediols and pregnanolones are conjugated in the liver to glucuronide and sulfate metabolites. Progesterone metabolites which are excreted in the bile may be deconjugated and may be further metabolized in the gut via reduction, dehydroxylation, and epimerization.

Excretion: The glucuronide and sulfate conjugates of pregnanediol and pregnanolone are excreted in the bile and urine. Progesterone metabolites which are excreted in the bile may undergo enterohepatic recycling or may be excreted in the feces.

Special Populations: The pharmacokinetics of PROMETRIUM Capsules have not been assessed in low body weight or obese patients.

Race: There is insufficient information available from trials conducted with PROMETRIUM Capsules to compare progesterone pharmacokinetics in different racial groups.

Hepatic Insufficiency: No formal studies have evaluated the effect of hepatic disease on the disposition of progesterone. However, since progesterone is metabolized by the liver, use in patients with severe liver dysfunction or disease is contraindicated. (See CONTRAINDICATIONS.) If treatment with progesterone is indicated in patients with mild to moderate hepatic dysfunction, these patients should be monitored carefully.

Renal Insufficiency: No formal studies have evaluated the effect of renal disease on the disposition of progesterone. Since progesterone metabolites are eliminated mainly by the kidneys, PROMETRIUM Capsules should be used with caution and only with careful monitoring in patients with renal dysfunction. (See PRECAUTIONS.)

Food–Drug Interaction: Concomitant food ingestion increased the bioavailability of PROMETRIUM Capsules relative to a fasting state when administered to postmenopausal women at a dose of 200 mg.

Drug–Drug Interaction: The metabolism of progesterone by human liver microsomes was inhibited by ketoconazole (IC50 less than 0.1 μM). Ketoconazole is a known inhibitor of cytochrome P450 3A4, hence these data suggest that ketoconazole or other known inhibitors of this enzyme may increase the bioavailability of progesterone. The clinical relevance of the in vitro findings is unknown.

Coadministration of conjugated estrogens and PROMETRIUM Capsules to 29 postmenopausal women over a 12-day period resulted in an increase in total estrone concentrations (Cmax 3.68 ng/mL to 4.93 ng/mL) and total equilin concentrations (Cmax 2.27 ng/mL to 3.22 ng/mL) and a decrease in circulating 17β estradiol concentrations (Cmax 0.037 ng/mL to 0.030 ng/mL). The half-life of the conjugated estrogens was similar with coadministration of PROMETRIUM Capsules. Table 2 summarizes the pharmacokinetic parameters.

TABLE 2 Mean (± S.D.) Pharmacokinetic Parameters for Estradiol, Estrone, and Equilin Following Coadministration of Conjugated Estrogens 0.625 mg and PROMETRIUM Capsules 200 mg for 12 Days to Postmenopausal Women
 | Conjugated Estrogens | Conjugated Estrogens plus PROMETRIUM Capsules
Drug | Cmax (ng/mL) | Tmax (hr) | AUC(0-24h) (ng•h/mL) | Cmax (ng/mL) | Tmax (hr) | AUC(0-24h) (ng•h/mL)
Estradiol | 0.037 ± 0.048 | 12.7 ± 9.1 | 0.676 ± 0.737 | 0.030 ± 0.032 | 17.32 ± 1.21 | 0.561 ± 0.572
Estrone Totala | 3.68 ± 1.55 | 10.6 ± 6.8 | 61.3 ± 26.36 | 4.93 ± 2.07 | 7.5 ± 3.8 | 85.9 ± 41.2
Equilin Totala | 2.27 ± 0.95 | 6.0 ± 4.0 | 28.8 ± 13.0 | 3.22 ± 1.13 | 5.3 ± 2.6 | 38.1 ± 20.2

a Total estrogens is the sume of conjugated and unconjugated estrogen.

Clinical Studies

Endometrial Protection: In a randomized, double-blind clinical trial, 358 postmenopausal women, each with an intact uterus, received treatment for up to 36 months. The treatment groups were: PROMETRIUM Capsules at the dose of 200 mg/day for 12 days per 28-day cycle in combination with conjugated estrogens 0.625 mg/day (n=120); conjugated estrogens 0.625 mg/day only (n=119); or placebo (n=119). The subjects in all three treatment groups were primarily Caucasian women (87% or more of each group). The results for the incidence of endometrial hyperplasia in women receiving up to 3 years of treatment are shown in Table 3. A comparison of the PROMETRIUM Capsules plus conjugated estrogens treatment group to the conjugated estrogens only group showed a significantly lower rate of hyperplasia (6% combination product vs. 64% estrogen alone) in the PROMETRIUM Capsules plus conjugated estrogens treatment group throughout 36 months of treatment.

TABLE 3 Incidence of Endometrial Hyperplasia in Women Receiving 3 Years of Treatment
Endometrial Diagnosis |  | Treatment Group
 | Conjugated Estrogens 0.625 mg + PROMETRIUM Capsules 200 mg (cyclical) | Conjugated Estrogens 0.625 mg (only) | Placebo
 | Number of patients | % of patients | Number of patients | % of patients | Number of patients | % of patients
 | n=117 | n=115 | n=116
HYPERPLASIAa | 7 | 6 | 74 | 64 | 3 | 3
Adenocarcinoma | 0 | 0 | 0 | 0 | 1 | 1
Atypical hyperplasia | 1 | 1 | 14 | 12 | 0 | 0
Complex hyperplasia | 0 | 0 | 27 | 23 | 1 | 1
Simple hyperplasia | 6 | 5 | 33 | 29 | 1 | 1

a Most advanced result to least advanced result:
Adenocarcinoma > atypical hyperplasia > complex hyperplasia > simple hyperplasia
The times to diagnosis of endometrial hyperplasia over 36 months of treatment are shown in Figure 1. This figure illustrates graphically that the proportion of patients with hyperplasia was significantly greater for the conjugated estrogens group (64%) compared to the conjugated estrogens plus PROMETRIUM Capsules group (6%).
Figure 1 Time to Hyperplasia in Women Receiving up to 36 Months of Treatment

The discontinuation rates due to hyperplasia over the 36 months of treatment are as shown in Table 4. For any degree of hyperplasia, the discontinuation rate for patients who received conjugated estrogens plus PROMETRIUM Capsules was similar to that of the placebo only group, while the discontinuation rate for patients who received conjugated estrogens alone was significantly higher. Women who permanently discontinued treatment due to hyperplasia were similar in demographics to the overall study population.

TABLE 4 Discontinuation Rate Due to Hyperplasia Over 36 Months of Treatment
Most Advanced Biopsy Result Through 36 Months of Treatment | Treatment Group
 | Conjugated Estrogens + PROMETRIUM Capsules (cyclical) | Conjugated Estrogens (only) | Placebo
 | n=120 | n=119 | n=119
 | Number of patients | % of patients | Number of patients | % of patients | Number of patients | % of patients
Adenocarcinoma | 0 | 0 | 0 | 0 | 1 | 1
Atypical hyperplasia | 1 | 1 | 10 | 8 | 0 | 0
Complex hyperplasia | 0 | 0 | 21 | 18 | 1 | 1
Simple hyperplasia | 1 | 1 | 13 | 11 | 0 | 0

In the same 3-year clinical trial, postmenopausal women were treated with PROMETRIUM Capsules in combination with conjugated estrogens, conjugated estrogens only, or placebo. There was no statistically significant difference between the PROMETRIUM Capsules plus conjugated estrogens group and the conjugated estrogens only group in increases of HDL-C and triglycerides, or in decreases of LDL-C. The changes observed in lipid profiles are shown in Table 5.

TABLE 5 Mean Changes from Baseline in Lipid Profiles After 36 Months of Treatment
Parameter | Treatment Group Mean (Mean % Change)
 | Conjugated Estrogens 0.625 mg + PROMETRIUM Capsules 200 mg (cyclical)a | Conjugated Estrogens 0.625 mg (only) | Placebo
 | n= 176 to 177b | n=171 to 173b | n=171
 | Mean Change | Mean % Change | Mean Change | Mean % Change | Mean Change | Mean % Change
LIPID PROFILE
HDL-C(mmol/L) | 0.07 | 5.1 | 0.10 | 7.2 | -0.05 | -2
LDL-C(mmol/L) | -0.43 | -11.8 | -0.36 | -9.5 | -0.14 | -2.9
Cholesterol (mmol/L) | -0.26 | -4.0 | -0.22 | -3.6 | -0.15 | -1.8
Triglyceride (mmol/L)c | 0.20 | 17.8 | 0.15 | 13.7 | 0.01 | 0.6

a There are no significant changes (p less than 0.05) from conjugated estrogens values.
b Number of subjects (n) varies by parameter.
c Computed from log transformed data.

Secondary Amenorrhea: In a single-center, randomized, double-blind clinical study that included premenopausal women with secondary amenorrhea for at least 90 days, administration of 10 days of PROMETRIUM Capsules therapy resulted in 80% of women experiencing withdrawal bleeding within 7 days of the last dose of PROMETRIUM Capsules, 300 mg/day (n=20), compared to 10% of women experiencing withdrawal bleeding in the placebo group (n=21).

The rate of secretory transformation was evaluated in a multicenter, randomized, double-blind clinical study in estrogen-primed postmenopausal women. PROMETRIUM Capsules administered orally for 10 days at 400 mg/day (n=22) induced complete secretory changes in the endometrium in 45% of women compared to 0% in the placebo group (n=23).

Women's Health Initiative Studies

The Women's Health Initiative (WHI) enrolled a total of 27,000 predominantly healthy postmenopausal women to assess the risks and benefits of either the use of oral 0.625 mg conjugated estrogens (CE) per day alone or the use of oral 0.625 mg conjugated estrogens plus 2.5 mg medroxyprogesterone acetate (MPA) per day compared to placebo in the prevention of certain chronic diseases. The primary endpoint was the incidence of coronary heart disease (CHD) (nonfatal myocardial infarction and CHD death), with invasive breast cancer as the primary adverse outcome studied. A “global index” included the earliest occurrence of CHD, invasive breast cancer, stroke, pulmonary embolism (PE), endometrial cancer, colorectal cancer, hip fracture, or death due to other cause. The study did not evaluate the effects of CE or CE/MPA on menopausal symptoms.

The CE/MPA substudy was stopped early because, according to the predefined stopping rule, the increased risk of breast cancer and cardiovascular events exceeded the specified benefits included in the “global index.” Results of the CE/MPA substudy, which included 16,608 women (average age of 63 years, range 50 to 79; 83.9% White, 6.5% Black, 5.5% Hispanic), after an average follow-up of 5.2 years are presented in Table 6 below.

TABLE 6 Relative and Absolute Risk Seen in the CE/MPA Substudy of WHIa
Eventc | Relative Risk CE/MPA vs. placebo at 5.2 Years (95% CI*) | Placebo n = 8102 | CE/MPA n = 8506
Absolute Risk per
10,000 Women-years
CHD events | 1.29 (1.02-1.63) | 30 | 37
Non-fatal MI | 1.32 (1.02-1.72) | 23 | 30
CHD death | 1.18 (0.70-1.97) | 6 | 7
Invasive breast cancerb | 1.26 (1.00-1.59) | 30 | 38
Stroke | 1.41 (1.07-1.85) | 21 | 29
Pulmonary embolism | 2.13 (1.39-3.25) | 8 | 16
Colorectal cancer | 0.63 (0.43-0.92) | 16 | 10
Endometrial cancer | 0.83 (0.47-1.47) | 6 | 5
Hip fracture | 0.66 (0.45-0.98) | 15 | 10
Death due to causes other than the events above | 0.92 (0.74-1.14) | 40 | 37
Global Index c | 1.15 (1.03-1.28) | 151 | 170
Deep vein thrombosis d | 2.07 (1.49-2.87) | 13 | 26
Vertebral fractures d | 0.66 (0.44-0.98) | 15 | 9
Other osteoporotic fractures d | 0.77 (0.69-0.86) | 170 | 131

a adapted from JAMA, 2002; 288:321-333
b includes metastatic and non-metastatic breast cancer with the exception of in situ breast cancer
c a subset of the events was combined in a “global index,” defined as the earliest occurrence of CHD events, invasive breast cancer, stroke, pulmonary embolism, endometrial cancer, colorectal cancer, hip fracture, or death due to other causes
d not included in Global Index
* nominal confidence intervals unadjusted for multiple looks and multiple comparisons

For those outcomes included in the "global index," the absolute excess risks per 10,000 women-years in the group treated with CE/MPA were 7 more CHD events, 8 more strokes, 8 more PEs, and 8 more invasive breast cancers, while the absolute risk reductions per 10,000 women-years were 6 fewer colorectal cancers and 5 fewer hip fractures. The absolute excess risk of events included in the “global index” was 19 per 10,000 women-years. There was no difference between the groups in terms of all-cause mortality. (See BOXED WARNINGS, WARNINGS, and PRECAUTIONS.)

Women's Health Initiative Memory Study

The Women's Health Initiative Memory Study (WHIMS), a substudy of WHI, enrolled 4,532 predominantly healthy postmenopausal women 65 years of age and older (47% were age 65 to 69 years, 35% were 70 to 74 years, and 18% were 75 years of age and older) to evaluate the effects of CE/MPA (0.625 mg conjugated estrogens plus 2.5 mg medroxyprogesterone acetate) on the incidence of probable dementia (primary outcome) compared with placebo.

After an average follow-up of 4 years, 40 women in the estrogen/progestin group (45 per 10,000 women-years) and 21 in the placebo group (22 per 10,000 women-years) were diagnosed with probable dementia. The relative risk of probable dementia in the hormone therapy group was 2.05 (95% CI, 1.21 to 3.48) compared to placebo. Differences between groups became apparent in the first year of treatment. It is unknown whether these findings apply to younger postmenopausal women. (See BOXED WARNINGS and WARNINGS, Dementia.)

INDICATIONS AND USAGE

PROMETRIUM Capsules are indicated for use in the prevention of endometrial hyperplasia in nonhysterectomized postmenopausal women who are receiving conjugated estrogens tablets. They are also indicated for use in secondary amenorrhea.

CONTRAINDICATIONS

PROMETRIUM Capsules should not be used in women with any of the following conditions:

1. PROMETRIUM Capsules should not be used in patients with known hypersensitivity to its ingredients. PROMETRIUM Capsules contain peanut oil and should never be used by patients allergic to peanuts.
2. Undiagnosed abnormal genital bleeding.
3. Known, suspected, or history of cancer of the breast.
4. Active deep vein thrombosis, pulmonary embolism or history of these conditions.
5. Active or recent (e.g., within the past year) arterial thromboembolic disease (e.g., stroke, myocardial infarction).
6. Liver dysfunction or disease.
7. Known or suspected pregnancy. There is no indication for PROMETRIUM Capsules in pregnancy. There appears to be little or no increased risk of birth defects in children born to women who have used estrogens and progestins from oral contraceptives inadvertently during early pregnancy. (See PRECAUTIONS.)

WARNINGS

See BOXED WARNINGS.

Cardiovascular Disorders

Estrogen with progestin therapy has been associated with an increased risk of cardiovascular events such as myocardial infarction and stroke, as well as venous thrombosis and pulmonary embolism (venous thromboembolism or VTE). Should any of these occur or be suspected, estrogen with progestin should be discontinued immediately.

Risk factors for arterial vascular disease (e.g., hypertension, diabetes mellitus, tobacco use, hypercholesterolemia, and obesity) and/or venous thromboembolism (e.g., personal history or family history of VTE, obesity, and systemic lupus erythematosus) should be managed appropriately.

Coronary Heart Disease and Stroke: In the Women's Health Initiative (WHI) study, an increase in the number of strokes was observed in women receiving CE compared to placebo.

In the CE/MPA substudy of WHI, an increased risk of coronary heart disease (CHD) events (defined as nonfatal myocardial infarction and CHD death) was observed in women receiving CE/MPA compared to women receiving placebo (37 vs. 30 per 10,000 women-years). The increase in risk was observed in year one and persisted. (See CLINICAL PHARMACOLOGY, Clinical Studies.)

In the same substudy of WHI, an increased risk of stroke was observed in women receiving CE/MPA compared to women receiving placebo (29 vs. 21 per 10,000 women-years). The increase in risk was observed after the first year and persisted. (See CLINICAL PHARMACOLOGY, Clinical Studies.)

In postmenopausal women with documented heart disease (n = 2,763, average age 66.7 years) a controlled clinical trial of secondary prevention of cardiovascular disease (Heart and Estrogen/Progestin Replacement Study; HERS) treatment with CE/MPA (0.625 mg/2.5 mg per day) demonstrated no cardiovascular benefit. During an average follow-up of 4.1 years, treatment with CE/MPA did not reduce the overall rate of CHD events in postmenopausal women with established coronary heart disease. There were more CHD events in the CE/MPA-treated group than in the placebo group in year 1, but not during the subsequent years. Two thousand three hundred and twenty one women from the original HERS trial agreed to participate in an open-label extension of HERS, HERS II. Average follow-up in HERS II was an additional 2.7 years, for a total of 6.8 years overall. Rates of CHD events were comparable among women in the CE/MPA group and the placebo group in HERS, HERS II, and overall.

Large doses of estrogen (5 mg conjugated estrogens per day), comparable to those used to treat cancer of the prostate and breast, have been shown in a large prospective clinical trial in men to increase the risks of nonfatal myocardial infarction, pulmonary embolism, and thrombophlebitis.

Venous Thromboembolism (VTE.): In the Women's Health Initiative (WHI) study, an increase in VTE was observed in women receiving CE compared to placebo.

In the CE/MPA substudy of WHI, a 2-fold greater rate of VTE, including deep venous thrombosis and pulmonary embolism, was observed in women receiving CE/MPA compared to women receiving placebo. The rate of VTE was 34 per 10,000 women-years in the CE/MPA group compared to 16 per 10,000 women-years in the placebo group. The increase in VTE risk was observed during the first year and persisted. (See CLINICAL PHARMACOLOGY, Clinical Studies.)

If feasible, estrogens with progestins should be discontinued at least 4 to 6 weeks before surgery of the type associated with an increased risk of thromboembolism, or during periods of prolonged immobilization.

Breast Cancer

The use of estrogens and progestins by postmenopausal women has been reported to increase the risk of breast cancer. The most important randomized clinical trial providing information about this issue is the Women's Health Initiative (WHI) substudy of CE/MPA. (See CLINICAL PHARMACOLOGY, Clinical Studies.) The results from observational studies are generally consistent with those of the WHI clinical trial and report no significant variation in the risk of breast cancer among different estrogens or progestins, doses, or routes of administration.

The CE/MPA substudy of WHI reported an increased risk of breast cancer in women who took CE/MPA for a mean follow-up of 5.6 years. Observational studies have also reported an increased risk for estrogen/progestin combination therapy, and a smaller increased risk for estrogen alone therapy, after several years of use. In the WHI trial and from observational studies, the excess risk increased with duration of use. From observational studies, the risk appeared to return to baseline in about five years after stopping treatment. In addition, observational studies suggest that the risk of breast cancer was greater, and became apparent earlier, with estrogen/progestin combination therapy as compared to estrogen alone therapy.

In the CE/MPA substudy, 26% of the women reported prior use of estrogen alone and/or estrogen/progestin combination hormone therapy. After a mean follow-up of 5.6 years during the clinical trial, the overall relative risk of invasive breast cancer was 1.24 (95% confidence interval 1.01-1.54), and the overall absolute risk was 41 vs. 33 cases per 10,000 women-years, for CE/MPA compared with placebo. Among women who reported prior use of hormone therapy, the relative risk of invasive breast cancer was 1.86, and the absolute risk was 46 vs. 25 cases per 10,000 women-years, for CE/MPA compared with placebo. Among women who reported no prior use of hormone therapy, the relative risk of invasive breast cancer was 1.09, and the absolute risk was 40 vs. 36 cases per 10,000 women-years for CE/MPA compared with placebo. In the same substudy, invasive breast cancers were larger and diagnosed at a more advanced stage in the CE/MPA group compared with the placebo group. Metastatic disease was rare with no apparent difference between the two groups. Other prognostic factors such as histologic subtype, grade and hormone receptor status did not differ between the groups.

The use of estrogen plus progestin has been reported to result in an increase in abnormal mammograms requiring further evaluation. All women should receive yearly breast examinations by a healthcare provider and perform monthly breast self-examinations. In addition, mammography examinations should be scheduled based on patient age, risk factors, and prior mammogram results.

Vision Disorders

Discontinue medication pending examination if there is sudden partial or complete loss of vision, or if there is a sudden onset of proptosis, diplopia or migraine. If examination reveals papilledema or retinal vascular lesions, medication should be withdrawn.

Dementia

In the Women's Health Initiative Memory Study (WHIMS), 4,532 generally healthy postmenopausal women 65 years of age and older were studied, of whom 35% were 70 to 74 years of age and 18% were 75 or older. After an average follow-up of 4 years, 40 women being treated with CE/MPA (1.8%, n = 2,229) and 21 women in the placebo group (0.9%, n = 2,303) received diagnoses of probable dementia. The relative risk for CE/MPA vs. placebo was 2.05 (95% confidence interval 1.21 – 3.48), and was similar for women with and without histories of menopausal hormone use before WHIMS. The absolute risk of probable dementia for CE/MPA vs. placebo was 45 vs. 22 cases per 10,000 women-years, and the absolute excess risk for CE/MPA was 23 cases per 10,000 women-years. It is unknown whether these findings apply to younger postmenopausal women. (See CLINICAL PHARMACOLOGY, Clinical Studies and PRECAUTIONS, Geriatric Use.)

PRECAUTIONS

Use of estrogens with a progestin may increase the risk of breast cancer compared to estrogen alone.

Ovarian Cancer

The CE/MPA substudy of WHI reported that estrogen plus progestin increased the risk of ovarian cancer. After an average follow-up of 5.6 years, the relative risk for ovarian cancer for CE/MPA vs. placebo was 1.58 (95% confidence interval 0.77 – 3.24) but was not statistically significant. The absolute risk for CE/MPA vs. placebo was 4.2 vs. 2.7 cases per 10,000 women-years. In some epidemiologic studies, the use of estrogen alone, in particular for ten or more years, has been associated with an increased risk of ovarian cancer. Other epidemiologic studies have not found these associations.

General

1. The pretreatment physical examination should include special reference to breast and pelvic organs, as well as Papanicolaou smear.
2. Because progesterone may cause some degree of fluid retention, conditions which might be influenced by this factor, such as epilepsy, migraine, asthma, cardiac or renal dysfunction, require careful observation.
3. In cases of breakthrough bleeding, as in any cases of irregular vaginal bleeding, nonfunctional causes should be considered. In cases of undiagnosed vaginal bleeding, adequate diagnostic measures are indicated.
4. Patients who have a history of clinical depression should be carefully observed and the drug discontinued if the depression recurs to a serious degree.
5. Further studies are needed to determine any possible influence of prolonged progestin therapy on pituitary, ovarian, adrenal, hepatic or uterine functions.
6. Although concomitant use of conjugated estrogens and PROMETRIUM Capsules did not result in a decrease in glucose tolerance, diabetic patients should be carefully observed while receiving estrogen-progestin therapy.
7. The pathologist should be advised of progestin therapy when relevant specimens are submitted.
8. Because of the occurrence of thrombotic disorders (thrombophlebitis, pulmonary embolism, retinal thrombosis, and cerebrovascular disorders) in patients taking estrogen-progestin combinations, the healthcare provider should be alert to the earliest manifestation of these disorders.
9. Transient dizziness may occur in some patients. Use caution when driving a motor vehicle or operating machinery. A small percentage of women may experience the following symptoms upon initial therapy: extreme dizziness and/or drowsiness, blurred vision, slurred speech, difficulty walking, loss of consciousness, vertigo, confusion, disorientation, feeling drunk, and shortness of breath. For these women, consultation with their healthcare provider regarding their treatment is advised. Bedtime dosing may alleviate these symptoms.
10. Rare instances of syncope and hypotension of possible orthostatic origin have been observed in patients taking PROMETRIUM Capsules.

Information for the Patient

See accompanying Patient Insert.

General: This product contains peanut oil and should not be used if you are allergic to peanuts.

Drug/Laboratory Test Interactions

The following laboratory results may be altered by the use of estrogen-progestin combination drugs:

- Increased sulfobromophthalein retention and other hepatic function tests.
- Coagulation tests: increase in prothrombin factors VII, VIII, IX and X.
- Metyrapone test.
- Pregnanediol determination.
- Thyroid function: increase in PBI, and butanol extractable protein bound iodine and decrease in T3 uptake values.

Fasting and 2-hour plasma insulin and glucose levels following an oral glucose tolerance test (OGTT) and fibrinogen levels were measured in patients receiving PROMETRIUM Capsules at a dose of 200 mg/day for 12 days per 28-day cycle in combination with conjugated estrogens 0.625 mg/day (n=120). Table 7 summarizes these data. Plasma insulin levels 2 hours post-OGTT were decreased from baseline. The fasting plasma glucose and fasting plasma insulin levels were also decreased from baseline. Glucose levels 2 hours post-OGTT were increased slightly. There was no effect on fibrinogen levels.

For information on changes in lipid profile, see the Clinical Studies subsection, Table 5.

TABLE 7 Mean Changes from Baseline in Insulin and Glucose Levels After 36 Months of Treatment
Parameter | Treatment Group Mean (Mean % Change)
 | Conjugated Estrogens 0.625 mg + PROMETRIUM Capsules 200 mg (cyclical)a | Conjugated Estrogens 0.625 mg (only) | Placebo
 | n= 173 to 176b | n=170 to 172b | n=171
 | Mean Change | Mean % Change | Mean Change | Mean % Change | Mean Change | Mean % Change
OGTT Insulin (pmol/L) | fasting 2 hours | -2.2 -45.2 | -6.2 -14.5 | -1.1 -23.9 | -3.2 -7.9 | 5.1 -29.7 | 14.2 -9.1
Glucose (mg/dL) | fasting 2 hours | -3.0 3.6 | -2.9 5.2 | -2.7 5.0 | -2.7 7.8 | -1.0 2.1 | -0.9 3.9

a There are no significant changes (p less than 0.05) from conjugated estrogens values.
b Number of subjects (n) varies by parameter.

Carcinogenesis, Mutagenesis, Impairment of Fertility

Progesterone has not been tested for carcinogenicity in animals by the oral route of administration. When implanted into female mice, progesterone produced mammary carcinomas, ovarian granulosa cell tumors and endometrial stromal sarcomas. In dogs, long-term intramuscular injections produced nodular hyperplasia and benign and malignant mammary tumors. Subcutaneous or intramuscular injections of progesterone decreased the latency period and increased the incidence of mammary tumors in rats previously treated with a chemical carcinogen.

Progesterone did not show evidence of genotoxicity in in vitro studies for point mutations or for chromosomal damage. In vivo studies for chromosome damage have yielded positive results in mice at oral doses of 1000 mg/kg and 2000 mg/kg. Exogenously administered progesterone has been shown to inhibit ovulation in a number of species and it is expected that high doses given for an extended duration would impair fertility until the cessation of treatment.

Pregnancy Category B

Reproductive studies have been performed in mice at doses up to 9 times the human oral dose, in rats at doses up to 44 times the human oral dose, in rabbits at a dose of 10 mcg/day delivered locally within the uterus by an implanted device, in guinea pigs at doses of approximately one-half the human oral dose and in rhesus monkeys at doses approximately the human dose, all based on body surface area, and have revealed little or no evidence of impaired fertility or harm to the fetus due to progesterone.

Rare cases of congenital anomalies including cleft palate, cleft lip, hypospadia, ventricular septal defect, patent ductus arteriosus, and other congenital heart defects have been reported in the infants of women using progesterone, including PROMETRIUM Capsules, in early pregnancy. Definitive causality has not been established. Rare instances of fetal death and spontaneous abortion have been reported in pregnant women prescribed PROMETRIUM Capsules for unapproved indications including the prevention of such outcomes. Studies in humans cannot rule out the possibility of harm. Therefore, PROMETRIUM Capsules should be used during pregnancy only if indicated. (See CONTRAINDICATIONS.)

Nursing Mothers

The administration of any drug to nursing mothers should be done only when clearly necessary since many drugs are excreted in human milk. Detectable amounts of progestin have been identified in the milk of nursing mothers receiving progestins. Caution should be exercised when PROMETRIUM Capsules are administered to a nursing woman.

Pediatric Use

PROMETRIUM Capsules are not indicated in children.

Geriatric Use

Clinical studies of PROMETRIUM Capsules did not include sufficient numbers of subjects aged 65 and over to determine whether they respond differently from younger subjects. Other reported clinical experience has not identified differences in responses between the elderly and younger patients. In general, dose selection for an elderly patient should be cautious, usually starting at the low end of the dosing range, reflecting the greater frequency of decreased hepatic, renal, or cardiac function, and of concomitant disease or other drug therapy.

In the Women's Health Initiative Memory Study, including 4,532 women 65 years of age and older, followed for an average of 4 years, 82% (n = 3,729) were 65 to 74 while 18% (n = 803) were 75 and over. Most women (80%) had no prior hormone therapy use. Women treated with conjugated estrogens plus medroxyprogesterone acetate were reported to have a two-fold increase in the risk of developing probable dementia. Alzheimer's disease was the most common classification of probable dementia in both the conjugated estrogens plus medroxyprogesterone acetate group and the placebo group. Ninety percent of the cases of probable dementia occurred in the 54% of women that were older than 70. (See WARNINGS, Dementia.)

ADVERSE REACTIONS

See BOXED WARNINGS, WARNINGS, and PRECAUTIONS.

Because clinical trials are conducted under widely varying conditions, adverse reaction rates observed in the clinical trials of a drug cannot be directly compared to rates in the clinical trials of another drug and may not reflect the rates observed in practice. The adverse reaction information from clinical trials does, however, provide a basis for identifying the adverse events that appear to be related to drug use and for approximate rates.

Endometrial Protection: Table 8 lists adverse experiences which were reported in greater than or equal to 2% of patients (regardless of relationship to treatment) who received cyclic PROMETRIUM Capsules, 200 mg daily (12 days per calendar month cycle) with daily 0.625 mg conjugated estrogen, in a multicenter, randomized, double-blind, placebo-controlled clinical trial in 875 postmenopausal women.

TABLE 8 Adverse Experiences (≥2%) Reported in an 875 Patient Placebo-Controlled Trial in Postmenopausal Women Over a 3-Year Period [Percentage (%) of Patients Reporting]
 | PROMETRIUM Capsules 200 mg with Conjugated Estrogens 0.625 mg | Conjugated Estrogens 0.625 mg (only) | Placebo
 | (n=178) | (n=175) | (n=174)
Headache | 31 | 30 | 27
Breast Tenderness | 27 | 16 | 6
Joint Pain | 20 | 22 | 29
Depression | 19 | 18 | 12
Dizziness | 15 | 5 | 9
Abdominal Bloating | 12 | 10 | 5
Hot Flashes | 11 | 14 | 35
Urinary Problems | 11 | 10 | 9
Abdominal Pain | 10 | 13 | 10
Vaginal Discharge | 10 | 10 | 3
Nausea / Vomiting | 8 | 6 | 7
Worry | 8 | 5 | 4
Chest Pain | 7 | 4 | 5
Diarrhea | 7 | 7 | 4
Night Sweats | 7 | 5 | 17
Breast Pain | 6 | 6 | 2
Swelling of Hands and Feet | 6 | 9 | 9
Vaginal Dryness | 6 | 8 | 10
Constipation | 3 | 3 | 2
Breast Carcinoma | 2 | less than 1 | less than 1
Breast Excisional Biopsy | 2 | 1 | less than 1
Cholecystectomy | 2 | less than 1 | less than 1

Secondary Amenorrhea: Table 9 lists adverse experiences which were reported in greater than or equal to 5% of patients receiving PROMETRIUM Capsules, 400 mg/day, in a multicenter, randomized, double-blind, placebo-controlled clinical trial in estrogen-primed (6 weeks) postmenopausal women receiving conjugated estrogens 0.625 mg/day and cyclic (10 days per calendar month cycle) PROMETRIUM Capsules at a dose of 400 mg/day, for three cycles.

TABLE 9 Adverse Experiences (≥5%) Reported in Patients Using 400 mg/day in a Placebo-Controlled Trial in Estrogen-Primed Postmenopausal Women
Adverse Experience | PROMETRIUM Capsules 400 mg | Placebo
 | n=25 | n=24
 | Percentage (%) of Patients
Fatigue | 8 | 4
Headache | 16 | 8
Dizziness | 24 | 4
Abdominal Distention (Bloating) | 8 | 8
Abdominal Pain (Cramping) | 20 | 13
Diarrhea | 8 | 4
Nausea | 8 | 0
Back Pain | 8 | 8
Musculoskeletal Pain | 12 | 4
Irritability | 8 | 4
Breast Pain | 16 | 8
Infection Viral | 12 | 0
Coughing | 8 | 0

The most common adverse experiences reported in greater than or equal to 5% of patients in all PROMETRIUM Capsules dosage groups studied in this trial (100 mg/day to 400 mg/day) were: dizziness (16%), breast pain (11%), headache (10%), abdominal pain (10%), fatigue (9%), viral infection (7%), abdominal distention (6%), musculoskeletal pain (6%), emotional lability (6%), irritability (5%), and upper respiratory tract infection (5%).

Other adverse events reported in less than 5% of patients taking PROMETRIUM Capsules include:

Administration Site Conditions: edema, edema peripheral

Blood and Lymphatic System: lymphadenopathy

Cardiac Disorders: angina pectoris, palpitation

Ear and Labyrinth Disorders: earache

Eye Disorders: abnormal vision

Gastrointestinal System Disorders: constipation, dry mouth, dyspepsia, gastroenteritis, hemorrhagic rectum, hiatus hernia, vomiting

General Disorders: chest pain, fever

Infections: abscess, herpes simplex

Injury, Poisoning and Procedural Complications: accidental injury

Musculoskeletal and Connective Tissue Disorders: arthritis, leg cramps, muscle disorder, myalgia

Nervous System Disorders: hypertonia, impaired concentration, somnolence, speech disorder

Psychiatric Disorders: anxiety, confusion, insomnia, personality disorder

Renal and Urinary Disorders: urinary tract infection

Reproductive System Disorders: fungal vaginitis, leukorrhea, uterine fibroid, vaginal dryness, vaginitis

Respiratory System Disorders: bronchitis, nasal congestion, pharyngitis, pneumonitis, sinusitis

Skin and Subcutaneous Tissue Disorders: acne, verruca, wound debridement

Vascular Disorders: hypertension

The following adverse experiences have been reported with PROMETRIUM Capsules in other U.S. clinical trials: increased sweating, asthenia, tooth disorder, anorexia, increased appetite, nervousness, and breast enlargement.

In addition to the adverse events observed in clinical trials, the following spontaneous adverse events have been reported during the marketing of PROMETRIUM Capsules.

Cardiac Disorders: circulatory collapse, tachycardia

Congenital, Familial, and Genetic Disorders: cleft lip, cleft palate, congenital heart disease, patent ductus arteriosus, ventricular septal defect

Ear and Labyrinth Disorders: tinnitus, vertigo

Eye Disorders: blurred vision, diplopia, visual disturbance

Gastrointestinal Disorders: acute pancreatitis, dysphagia, swollen tongue

General Disorders and Administration Site Conditions: abnormal gait, difficulty walking, feeling abnormal, feeling drunk

Hepatobiliary Disorders: cholestasis, cholestatic hepatitis, jaundice, hepatitis, hepatic failure, hepatic necrosis, increased liver function tests

Immune System Disorders: anaphylactic reaction, hypersensitivity

Investigations: alanine aminotransferase increased, aspartate aminotransferase increased, gamma-glutamyl transferase increased, hepatic enzyme increased, blood glucose increased, weight decreased, weight increased

Musculoskeletal Disorders: arthralgia, muscle cramp

Neoplasms Benign, Malignant, and Unspecified: endometrial carcinoma

Nervous System Disorders: convulsion, depressed consciousness, dysarthria, loss of consciousness, paresthesia, sedation, stupor, syncope (with and without hypotension), transient ischemic attack

Pregnancy, Puerperium, and Perinatal Conditions: intra-uterine death, spontaneous abortion

Psychiatric Disorders: aggression, depersonalization, disorientation, suicidal ideation,

Reproductive System and Breast Disorders: menorrhagia, menstrual disorder, metrorrhagia, ovarian cyst

Respiratory, Thoracic, and Mediastinal Disorders: asthma, choking, dyspnea, face edema, throat tightness

Skin and Subcutaneous Tissue Disorders: alopecia, pruritus, urticaria

Vascular Disorders: hypertension, hypotension

The following additional adverse experiences have been observed in women taking estrogen and/or progestins in general: breakthrough bleeding, spotting, change in menstrual flow, amenorrhea, changes in weight (increase or decrease), changes in the cervical squamo-columnar junction and cervical secretions, cholestatic jaundice, anaphylactoid reactions and anaphylaxis, rash (allergic) with and without pruritus, melasma or chloasma, that may persist when drug is discontinued, dysmenorrhea, increase in size of uterine leiomyomata, ovarian cancer, endometrial hyperplasia, endometrial cancer, galactorrhea, nipple discharge, increased incidence of gallbladder disease, enlargement of hepatic hemangiomas, erythema multiforme, erythema nodosum, hirsutism, hemorrhagic eruption, intolerance to contact lenses, migraine, chorea, reduced carbohydrate tolerance, aggravation of porphyria, changes in libido, hypocalcemia, angioedema, exacerbation of asthma, increased triglycerides.

OVERDOSAGE

No studies on overdosage have been conducted in humans. In the case of overdosage, PROMETRIUM Capsules should be discontinued and the patient should be treated symptomatically.

DOSAGE AND ADMINISTRATION

Prevention of Endometrial Hyperplasia: PROMETRIUM Capsules should be given as a single daily dose at bedtime, 200 mg orally for 12 days sequentially per 28-day cycle, to postmenopausal women with a uterus who are receiving daily conjugated estrogens tablets.

Secondary Amenorrhea: PROMETRIUM Capsules may be given as a single daily dose of 400 mg at bedtime for 10 days.

Some women may experience difficulty swallowing PROMETRIUM Capsules. For these women, PROMETRIUM Capsules should be taken with a glass of water while in the standing position.

HOW SUPPLIED

PROMETRIUM® (progesterone, USP) Capsules 100 mg are round, peach-colored capsules branded with black imprint “SV.”

NDC 54868-4250-1 | Bottles of 10
NDC 54868-4250-0 | Bottles of 30

PROMETRIUM® (progesterone, USP) Capsules 200 mg are oval, pale yellow-colored capsules branded with black imprint “SV2.”

NDC 54868-4230-2 | Bottles of 5
NDC 54868-4230-1 | Bottles of 10
NDC 54868-4230-0 | Bottles of 30

Store at 25°C (77°F); excursions permitted to 15° to 30°C (59° to 86°F) [See USP Controlled Room Temperature].

Protect from excessive moisture.

Dispense in tight, light-resistant container as defined in USP/NF, accompanied by a Patient Insert.

Keep out of reach of children.

Manufactured by:
Catalent Pharma Solutions
St. Petersburg, FL 33716

Marketed by:
Solvay Pharmaceuticals, Inc.
Marietta, GA 30062

© 2008 Solvay Pharmaceuticals, Inc.
All rights reserved.

500032 Rev Jan 2008

500033 Rev Jan 2008

Relabeling and Repackaging by:
Physicians Total Care, Inc.
Tulsa, OK 74146

PATIENT INFORMATION
(Updated 02 Jan 2008)

PROMETRIUM® (progesterone, USP)
Capsules 100 mg
Capsules 200 mg

Rx only

Read this PATIENT INFORMATION before you start taking PROMETRIUM® Capsules and read what you get each time you refill PROMETRIUM Capsules, because there may be new information. This information does not take the place of talking to your healthcare provider about your medical condition or your treatment.

WHAT IS THE MOST IMPORTANT INFORMATION I SHOULD KNOW ABOUT PROMETRIUM CAPSULES (A Progesterone Hormone)?

- Progesterone with or without estrogens should not be used to prevent heart attacks or heart disease.
- Using estrogens with or without progestins may increase your chances of getting heart attacks, strokes, breast cancer, and blood clots. Using estrogens with progestins may increase your risk of dementia. You and your healthcare provider should talk regularly about whether you still need treatment with PROMETRIUM Capsules.

THIS PRODUCT CONTAINS PEANUT OIL AND SHOULD NOT BE USED IF YOU ARE ALLERGIC TO PEANUTS.

WHAT IS PROMETRIUM CAPSULES?

PROMETRIUM Capsules contain the female hormone called progesterone.

What is PROMETRIUM Capsules used for?

Treatment of Menstrual Irregularities

PROMETRIUM Capsules are used for the treatment of secondary amenorrhea (absence of menstrual periods in women who have previously had a menstrual period) due to a decrease in progesterone. When you do not produce enough progesterone, menstrual irregularities can occur. If your healthcare provider has determined your body does not produce enough progesterone on its own, PROMETRIUM Capsules may be prescribed to provide the progesterone you need.

Protection of the Endometrium (Lining of the Uterus)

PROMETRIUM Capsules are used in combination with estrogen-containing medications in postmenopausal women with a uterus. Taking estrogens alone increases the chance of developing a condition called endometrial hyperplasia, that may lead to cancer of the lining of the uterus. In general, the addition of a progestin is recommended for women with a uterus to reduce the chance of getting cancer of the uterus.

Who should not take PROMETRIUM Capsules?

Do not start taking PROMETRIUM Capsules if you:

- are allergic to peanuts.
- are allergic to progesterone, progesterone-like drugs, or any of the inactive ingredients in the capsules. See the end of this leaflet for a list of ingredients in PROMETRIUM Capsules.
- are pregnant or suspect that you are pregnant.
- have or have had blood clots in the legs, lungs, eyes, brain, or elsewhere.
- have liver disease.
- have known or suspected cancer of the breast or reproductive organs.
- have unusual bleeding from the vagina which has not been evaluated by your healthcare provider.
- have a miscarriage and your healthcare provider suspects some tissue is still in the uterus.
- are nursing.

Tell your healthcare provider:

- if you are breastfeeding. The hormones in PROMETRIUM Capsules can pass into your milk.
- about all of your medical problems. Your healthcare provider may need to check you more carefully if you have certain conditions, such as diabetes, asthma (wheezing), epilepsy (seizures), migraine, endometriosis, lupus, problems with your heart, liver, thyroid, kidneys, or have high calcium levels in your blood.
- about all the medicines you take. This includes prescription and nonprescription medicines, vitamins, and herbal supplements. Some medicines may affect how PROMETRIUM Capsules works. PROMETRIUM Capsules may also affect how your other medicines work.

How should I take PROMETRIUM Capsules?

1. Prevention of Endometrial Hyperplasia: Postmenopausal women with a uterus who are taking estrogens should take a single daily dose of 200 mg PROMETRIUM Capsules at bedtime for 12 continuous days per 28-day cycle.
2. Secondary Amenorrhea: PROMETRIUM Capsules may be given as a single daily dose of 400 mg at bedtime for 10 days.
3. PROMETRIUM Capsules are to be taken at bedtime as some women become very drowsy* and/or dizzy* after taking PROMETRIUM Capsules. In a small percentage of these women, these effects may be increased including blurred vision, difficulty speaking, difficulty walking, and feeling abnormal. If you experience these symptoms, discuss them with your healthcare provider immediately. Taking PROMETRIUM Capsules at bedtime may minimize the impact of these symptoms.

* Use caution when driving a motor vehicle or operating machinery as dizziness or drowsiness may occur.

If you experience difficulty in swallowing PROMETRIUM Capsules, it is recommended that you take your daily dose at bedtime with a glass of water while in the standing position.

What are the risks associated with PROMETRIUM Capsules?

- Risk to the Fetus: Rare cases of cleft palate, cleft lip, hypospadia, and congenital heart defects have been reported in the infants of women using progesterone, including PROMETRIUM Capsules during early pregnancy. Although it is not clear that these events were drug related, you should check with your healthcare provider about the risks to your unborn child of any medication taken during pregnancy.
- Abnormal Blood Clotting: Use of progestational drugs has been associated with changes in the blood-clotting system. These changes allow the blood to clot more easily, possibly allowing clots to form in the bloodstream. If blood clots do form in your bloodstream, they can cut off the blood supply to vital organs, causing serious problems. These problems may include a stroke (by cutting off blood to part of the brain), a heart attack (by cutting off blood to part of the heart), a pulmonary embolus (by cutting off blood to part of the lungs), visual loss or blindness (by cutting off blood vessels in the eye), or other problems. Any of these conditions may cause death or serious long-term disability. Call your healthcare provider immediately if you suspect you have any of these conditions. He or she may advise you to stop using this drug.
- Eye Abnormalities: Discontinue medication and call your healthcare provider immediately if you experience sudden partial or complete loss of vision, blurred vision, or sudden onset of bulging eyes, double vision, or migraine.

What are the possible side effects of PROMETRIUM Capsules?

Consult your healthcare provider if you experience any of the side effects mentioned below or other side effects.

SIDE EFFECTS REPORTED IN STUDIES OF PATIENTS AT DOSES OF 100 MG/DAY TO 400 MG/DAY:

Blood and Lymphatic System: swelling of the lymph nodes
Cardiovascular System: high blood pressure, hot flashes, pounding or racing of the heart
Digestive System: bloating, constipation, diarrhea, dry mouth, heartburn, indigestion, nausea/vomiting
General Disorders: abdominal pain (cramping), back pain, chest pain, fatigue, fever, fluid retention, headache, intestinal pain, stomach pain, swelling, swelling of the legs and arms
Infections: bronchitis, fungal vaginal infection, infections, inflammation of the vagina, upper respiratory tract infection, urinary tract infection, viral infection
Musculoskeletal System: arthritis, joint pain, muscle or bone pain, leg cramps, muscle cramps
Nervous/Psychiatric System: anxiety, confusion, decreased concentration, depression, dizziness*, drowsiness*, irritability, mood swings, personality disorder, sleep disorder, worry
Respiratory System: coughing, fluid in sinus cavities, nasal congestion, sore throat, fluid in the lungs
Reproductive System: breast pain, breast tenderness, vaginal discharge, vaginal dryness, uterine fibroid
Skin: acne, night sweats
Eyes: blurred vision
Kidney and Urinary System: urinary problems

* Use caution when driving a motor vehicle or operating machinery as dizziness or drowsiness may occur.

During the marketing of PROMETRIUM Capsules, other adverse events have been reported, including reversible cases of liver problems, particularly in patients taking high doses. Additionally, rare occurrences of fainting and/or low blood pressure have also been reported.

These are some of the warning signs of serious side effects:

Be alert for unusual signs and symptoms. If any of these warning signals (or any other unusual symptoms) happen while you are using PROMETRIUM Capsules, call your healthcare provider immediately:

- Breast lumps (Ask your healthcare provider to show you how to examine your breasts monthly.)
- Pain, swelling, or tenderness in the abdomen
- Tremors or seizures, migraine headaches, shortness of breath or asthma, heart problems, or kidney problems
- Abnormal bleeding from the vagina
- Feelings of depression
- Pains in the calves or chest; a sudden shortness of breath; or coughing blood, indicating possible clots in the legs, heart or lungs
- Severe headache, vomiting, dizziness, faintness, or changes in vision or speech; weakness or numbness in an arm or leg, indicating possible clots in the brain or eye

General information about safe and effective use of PROMETRIUM Capsules

- Medicines are sometimes prescribed for conditions that are not mentioned in patient information leaflets. Do not take PROMETRIUM Capsules for conditions for which it was not prescribed.
- Your healthcare provider has prescribed this drug for you and you alone. Do not give PROMETRIUM Capsules to other people, even if they have the same symptoms you have. It may harm them.
- PROMETRIUM Capsules should be taken as a single daily dose at bedtime. Some women may experience extreme dizziness and/or drowsiness during initial therapy. In a small percentage of women, these effects may be increased including blurred vision, difficulty speaking, difficulty walking, and feeling abnormal. If you experience these symptoms, discuss them with your healthcare provider immediately. A single bedtime dose may reduce the impact of these symptoms.
- Use caution when driving a motor vehicle or operating machinery as dizziness or drowsiness may occur.

Keep PROMETRIUM Capsules out of the reach of children.

This leaflet provides a summary of the most important information about PROMETRIUM Capsules. If you would like more information, talk with your healthcare provider or pharmacist. You can ask for information about PROMETRIUM Capsules that is written for health professionals. You can get more information by calling the toll free number 1-800-241-1643.

What are the ingredients in PROMETRIUM Capsules?

Active ingredient: 100 mg or 200 mg micronized progesterone

The inactive ingredients for PROMETRIUM Capsules 100 mg include: peanut oil NF, gelatin NF, glycerin USP, lecithin NF, titanium dioxide USP, D&C Yellow No. 10, and FD&C Red No. 40.

The inactive ingredients for PROMETRIUM Capsules 200 mg include: peanut oil NF, gelatin NF, glycerin USP, lecithin NF, titanium dioxide USP, D&C Yellow No. 10, and FD&C Yellow No. 6.

HOW SUPPLIED

PROMETRIUM Capsules 100 mg are round, peach-colored capsules branded with black imprint “SV.”

PROMETRIUM Capsules 200 mg are oval, pale yellow-colored capsules branded with black imprint “SV2.”

Store at 25°C (77°F); excursions permitted to 15° to 30°C (59° to 86°F) [See USP Controlled Room Temperature].

Protect from excessive moisture.

Manufactured by:
Catalent Pharma Solutions
St. Petersburg, FL 33716

Marketed by:
Solvay Pharmaceuticals, Inc.
Marietta, GA 30062

© 2008 Solvay Pharmaceuticals, Inc.
All rights reserved.

500033 Rev Jan 2008

PRINCIPAL DISPLAY PANEL

PROMETRIUM® (progesterone, USP) Capsules

100 mg

PROMETRIUM® (progesterone, USP) Capsules

200 mg